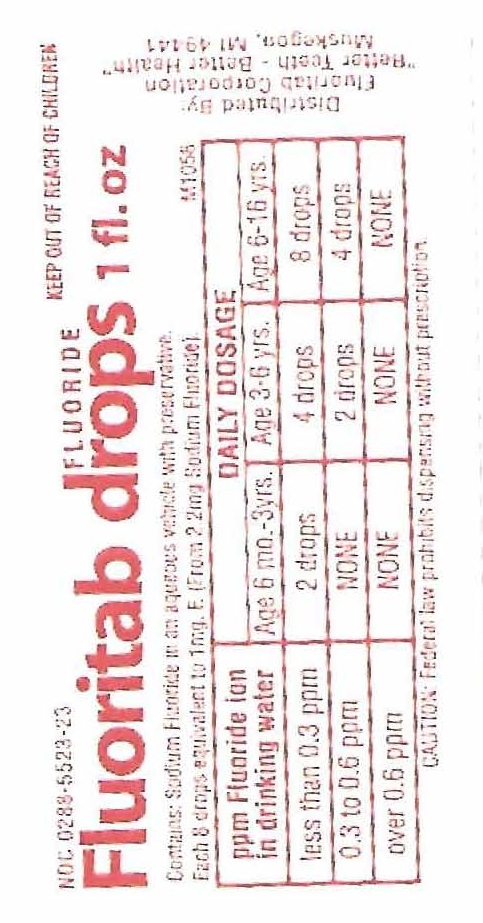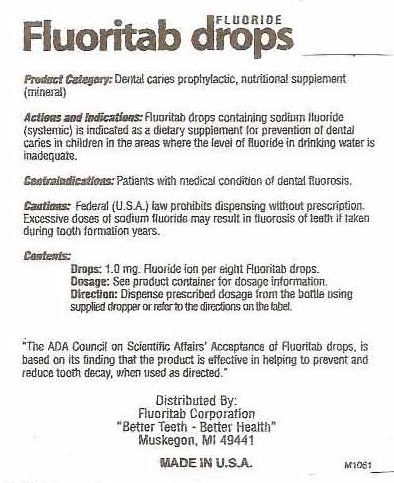 DRUG LABEL: FLUORIDE DROPS
								
NDC: 0288-5523 | Form: LIQUID
Manufacturer: Fluoritab Corporation
Category: prescription | Type: HUMAN PRESCRIPTION DRUG LABEL
Date: 20110505

ACTIVE INGREDIENTS: SODIUM FLUORIDE 2.5 mg/1 mL
INACTIVE INGREDIENTS: WATER; METHYLPARABEN

FLUORITAB FLUORIDE DROPS 1 fluid ounce size

ACTIVE INGREDIENT

CONTAINS: SODIUM FLUORIDE IN AN AQUEOUS VEHICLE WITH PRESERVATIVE.

EACH 8 DROPS EQUIVALENT TO 1 MG. F. (FROM 2.2 MG SODIUM FLUORIDE)

PPM FLUORIDE ION DAILY DOSAGE

IN DRINKING WATER AGE 6 MO. – 3 YRS. AGE 3-6 YRS. AGE 6-16 YRS.

LESS THAN 0.3 PPM 2 DROPS 4 DROPS 8 DROPS

0.3 TO 0.6 PPM NONE 2 DROPS 4 DROPS

OVER 0.6 PPM NONE NONE NONE

KEEP OUT OF REACH OF CHILDREN.

WARNINGS

CAUTION: FEDERAL (U.S.A.) LAW PROHIBITS DISPENSING WITHOUT PRESCRIPTION.

CONTRAINDICATIONS

CONTRAINDICATIONS: PATIENTS WITH MEDICAL CONDITION OF DENTAL FLUOROSIS.

PURPOSE

PRODUCT CATEGORY: DENTAL CARIES PROPHYLACTIC, NUTRITIONAL SUPPLEMENT (MINERAL)

INDICATIONS AND USAGE

ACTIONS AND INDICATIONS: FLUORITAB DROPS CONTAINING SODIUM FLUORIDE (SYSTEMIC) IS INDICATED AS A DIETARY SUPPLEMENT FOR PREVENTION OF DENTAL CARIES IN CHILDREN IN THE AREAS WHERE THE LEVEL OF FLUORIDE IN DRINKING WATER IS INADEQUATE.

INACTIVE INGREDIENTS: WATER, PRESERVATIVE.

WARNINGS AND PRECAUTIONS

EXCESSIVE DOSES OF SODIUM FLUORIDE MAY RESULT IN FLUOROSIS OF TEETH IF TAKEN DURING FORMATION YEARS.

PACKAGE LABEL

FLUORITAB FLUORIDE DROPS
DISTRIBUTED BY:
FLUORITAB CORPORATION
"BETTER TEETH - BETTER HEALTH"
MUSKEGON, MI 49441
MADE IN U.S.A.